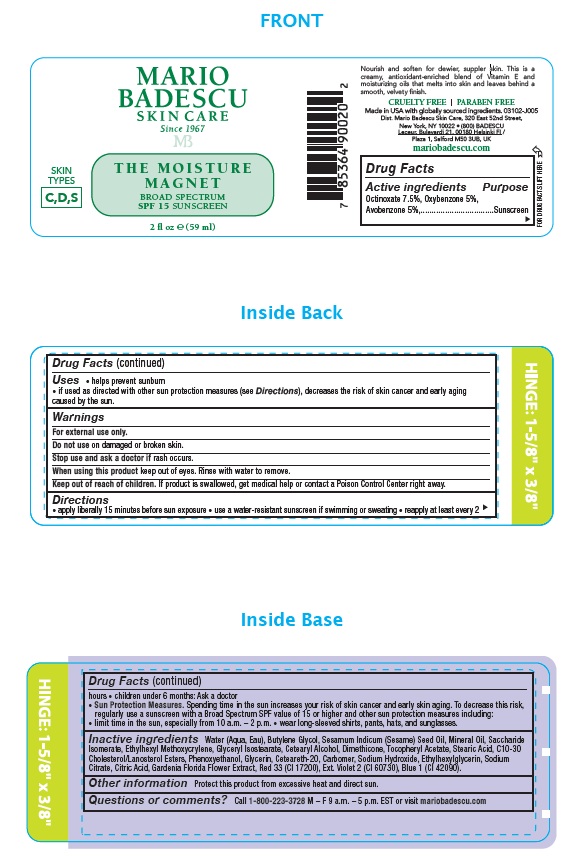 DRUG LABEL: Mario Badescu The Moisture Magnet SPF 15
NDC: 54111-191 | Form: LOTION
Manufacturer: Bentley Laboratories LLC
Category: otc | Type: HUMAN OTC DRUG LABEL
Date: 20260121

ACTIVE INGREDIENTS: OCTINOXATE 4.43 g/59 mL; OXYBENZONE 2.95 g/59 mL; AVOBENZONE 2.95 g/59 mL
INACTIVE INGREDIENTS: WATER; BUTYLENE GLYCOL; SESAME OIL; MINERAL OIL; SACCHARIDE ISOMERATE; ETHYLHEXYL METHOXYCRYLENE; GLYCERYL ISOSTEARATE; CETOSTEARYL ALCOHOL; DIMETHICONE; .ALPHA.-TOCOPHEROL ACETATE; STEARIC ACID; C10-30 CHOLESTEROL/LANOSTEROL ESTERS; PHENOXYETHANOL; GLYCERIN; CETEARETH-20; CARBOMER HOMOPOLYMER, UNSPECIFIED TYPE; SODIUM HYDROXIDE; ETHYLHEXYLGLYCERIN; SODIUM CITRATE; CITRIC ACID; GARDENIA JASMINOIDES FLOWER; RED 33; EXT. VIOLET 2; BLUE 1

MARIO BADESCU MOISTURE MAGNET SPF 15

DRUG FACTS

Active ingredients

Octinoxate 7.5%, Oxybenzone 5%, Avobenzone 5%

Purpose

Sunscreen

INDICATIONS AND USAGE

Uses • helps prevent sunburn
• If used as directed with other sun protection measures (see Directions), decreases the risk of skin cancer and early aging caused by the sun.

Warnings

For external use only.

Do not use on damaged or broken skin.

Stop use and ask a doctor if rash occurs.

When using this product keep out of eyes. Rinse with water to remove.

Keep out of reach of children. If product is swallowed, get medical help or contact a Poison Control Center right away.

Directions

• apply liberally 15 minutes before sun exposure • use a water-resistant sunscreen if swimming or sweating • reapply at least every 2 hours • children under 6 months: Ask a doctor
• Sun Protection Measures. Spending time in the sun increases your risk of skin cancer and early skin aging. To decrease this risk, regularly use a sunscreen with a Broad Spectrum SPF value of 15 or higher and other sun protection measures including:
• limit time in the sun, especially from 10 a.m. – 2 p.m. • wear long-sleeved shirts, pants, hats, and sunglasses.

INACTIVE INGREDIENT

Inactive ingredients Water (Aqua, Eau), Butylene Glycol, Sesamum Indicum (Sesame) Seed Oil, Mineral Oil, Saccharide
Isomerate, Ethylhexyl Methoxycrylene, Glyceryl Isostearate, Cetearyl Alcohol, Dimethicone, Tocopheryl Acetate, Stearic Acid, C10-30
Cholesterol/Lanosterol Esters, Phenoxyethanol, Glycerin, Ceteareth-20, Carbomer, Sodium Hydroxide, Ethylhexylglycerin, Sodium
Citrate, Citric Acid, Gardenia Florida Flower Extract, Red 33 (CI 17200), Ext. Violet 2 (CI 60730), Blue 1 (CI 42090).

Other information Protect this product from excessive heat and direct sun.

Questions or comments? Call 1-800-223-3728 M – F 9 a.m. – 5 p.m. EST or visit mariobadescu.com

Principal Display Panel

MARIO
BADESCU
SKIN CARE
Since 1967

THE MOISTURE
MAGNET
BROAD SPECTRUM
SPF 15 SUNSCREEN

2 fl oz ℮ (59 ml)

SKIN
TYPES
C,D,S

CRUELTY FREE | PARABEN FREE

Made in USA. 03102-J005

Dist. Mario Badescu Skin Care, 320 East 52nd Street,
New York, NY 10022 • (800) BADESCU
Leceur, Bulevardi 21, 00180 Helsinki FI /
Plaza 1, Salford M50 3UB, UK

mariobadescu.com

res